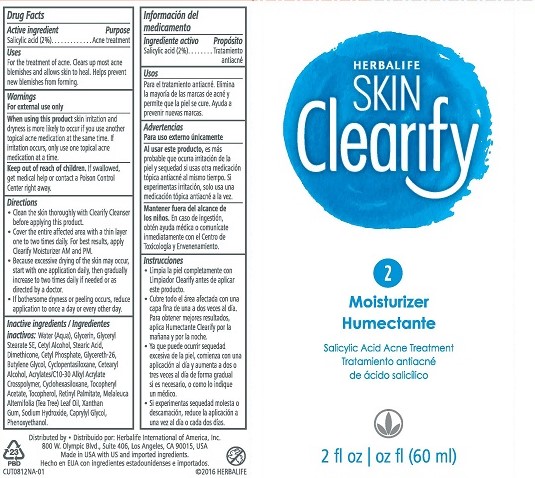 DRUG LABEL: Skin Clearify Moisturizer
NDC: 51785-812 | Form: LIQUID
Manufacturer: Herbalife International of America Inc.
Category: otc | Type: HUMAN OTC DRUG LABEL
Date: 20161010

ACTIVE INGREDIENTS: SALICYLIC ACID 2 g/100 mL
INACTIVE INGREDIENTS: DIMETHICONE; CARBOMER COPOLYMER TYPE A; GLYCERYL STEARATE SE; GLYCERETH-26; CETOSTEARYL ALCOHOL; VITAMIN A PALMITATE; SODIUM HYDROXIDE; PHENOXYETHANOL; WATER; BUTYLENE GLYCOL; XANTHAN GUM; CAPRYLYL GLYCOL; GLYCERIN; CETYL ALCOHOL; STEARIC ACID; CETYL PHOSPHATE; CYCLOMETHICONE 5; CYCLOMETHICONE 6; ALPHA-TOCOPHEROL ACETATE; TOCOPHEROL; TEA TREE OIL

Clearify Acne Moisturizer

Drug Facts

Active ingredient

Salicylic acid (2%)

Purpose

Acne treatment

Uses

For the treatment of acne. Clears up most acne blemishes and allows skin to heal. Helps prevent new blemishes from forming.

Warnings

For external use only

When using this product skin irritation and dryness is more likely to occur if you use another topical acne medication at the same time. If irritation occurs, only use one topical acne medication at a time.

Keep out of reach of children. If swallowed, get medical help or contact a Poison Control Center right away.

Directions

- Clean the skin thoroughly with Clearify Cleanser before applying this product.
- Cover the entire affected area with a thin layer one to two times daily. For best results, apply Clearify Moisturizer AM and PM.
- Because excessive drying of the skin may occur, start with one application daily, then gradually increase to two times daily if needed or as directed by a doctor.
- If bothersome dryness or peeling occurs, reduce application to once a day or every other day.

INACTIVE INGREDIENT

Inactive ingredients: Water (Aqua), Glycerin, Glyceryl Stearate SE, Cetyl Alcohol, Stearic Acid, Dimethicone, Cetyl Phosphate, Glycereth-26, Butylene Glycol, Cyclopentasiloxane, Cetearyl Alcohol, Acrylates/C10-30 Alkyl Acrylate Crosspolymer, Cyclohexasiloxane, Tocopheryl Acetate, Tocopherol, Retinyl Palmitate, Melaleuca Alternifolia (Tea Tree) Leaf Oil, Xanthan Gum, Sodium Hydroxide, Caprylyl Glycol, Phenoxyethanol.

Distributed by: Herbalife International of America, Inc.

800 W. Olympic Blvd., Suite 406, Los Angeles, CA 90015 USA

Made in USA with US and imported ingredients.

© 2016 HERBALIFE

PACKAGE LABEL

HERBALIFE

SKIN Clearify

2

Moisturizer

Salicylic Acid Acne Treatment

2 fl oz (60 mL)